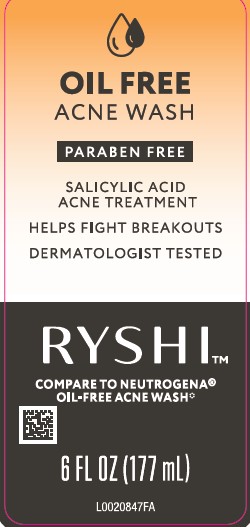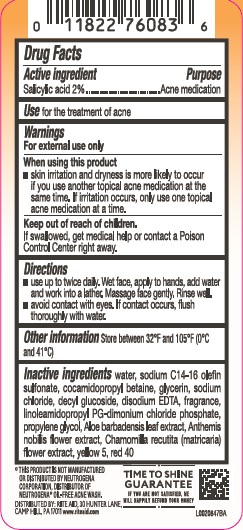 DRUG LABEL: Oil Free Acne Wash
NDC: 11822-0947 | Form: LOTION
Manufacturer: Rite Aid
Category: otc | Type: HUMAN OTC DRUG LABEL
Date: 20250411

ACTIVE INGREDIENTS: SALICYLIC ACID 20.6 mg/1 mL
INACTIVE INGREDIENTS: WATER; SODIUM C14-16 OLEFIN SULFONATE; COCAMIDOPROPYL BETAINE; GLYCERIN; SODIUM CHLORIDE; DECYL GLUCOSIDE; EDETATE DISODIUM ANHYDROUS; LINOLEAMIDOPROPYL PG-DIMONIUM CHLORIDE PHOSPHATE; PROPYLENE GLYCOL; ALOE VERA LEAF; CHAMAEMELUM NOBILE; CHAMOMILE; FD&C YELLOW NO. 5; FD&C RED NO. 40

Ryshi 947.003/947AC-AD
Oil Free Acne Wash

Active ingredient

Salicylic acid 2%

Purpose

Acne medication

Use

for the treatment of acne

Warnings

For external use only

When using this product

- skin irritation and dryness is more likely to occur if you use another topical acne medication at the same time. If irritation occurs, only use one topical acne medication at a time

Keep out of reach of children.

If swallowed, get medical help or contact a Poison Control Center right away.

Directions

- use twice a daily. Wet face, apply to hands, add water and work into lather. Massage face gently. Rinse well.
- avoid contact with eyes. If contact with eyes. If contact occurs, flush thoroughly with water.

Other Information

Store between 32°F and 105°F (0°C and 41°C)

Inactive ingredients

water, sodium C14-16 olefin sulfonate, cocamidopropyl betaine, glycerin, sodium chloride, decyl glucoside, disodium EDTA, fragrance, linoleamidopropyl PG-dimonium chloride phosphate, propylene glycol, Aloe barbadensis leaf extract, Anthemis nobilis flower extract, Chamomilla recutita (matricaria) flower extract, yellow 5, red 40

Disclaimer

*This product is not manufactured or distributed by Neutorgena Corporation, distributor of NEUTROGENAOil-Free Acne Wash.

ADVERSE REACTION

DISTRIBUTED BY: RITE AID

30 HUNTER LANE,

CAMP HILL, PA 17011 www.riteaid.com

TIME TO SHINE GUARANTEE

IF YOU ARE NOT SATISIFED, WE WILL HAPPILY REFUND YOUR MONEY.

principal display panel

Oil Free

Acne Wash

Paraben Free

Salicylic Acid

Acne Treatment

Helps fight breakouts

Dermatologist Tested

RYSHI™

Compare to NEUTROGENA®Oil-Free Acne Wash*

6 FL OZ (177 mL)